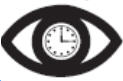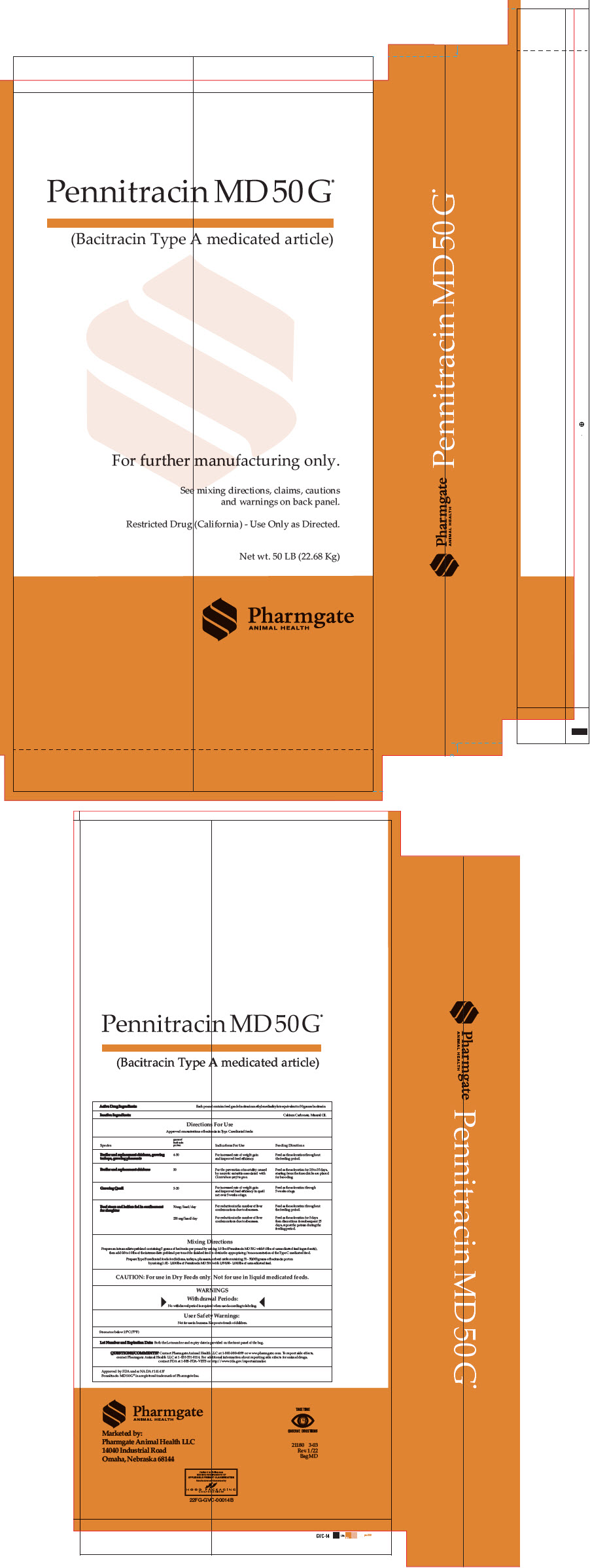 DRUG LABEL: Pennitracin MD 50G
NDC: 51429-054 | Form: GRANULE
Manufacturer: Pharmgate Animal Health
Category: animal | Type: OTC TYPE A MEDICATED ARTICLE ANIMAL DRUG LABEL
Date: 20240815

ACTIVE INGREDIENTS: Bacitracin Methylenedisalicylate 110 g/1 kg
INACTIVE INGREDIENTS: Calcium Carbonate; Mineral Oil

Pennitracin MD 50 G®
(Bacitracin Type A medicated article)

For further manufacturing only.

VETERINARY INDICATIONS

See mixing directions, claims, cautions and warnings on back panel.

Restricted Drug (California) - Use Only as Directed.

Net wt. 50 LB (22.68 Kg)

Pennitracin MD 50 G®

(Bacitracin Type A medicated article)

Active Drug Ingredients: Each pound contains feed grade bacitracin methylenedisalicylate equivalent to 50 grams bacitracin

Inactive Ingredients: Calcium Carbonate, Mineral Oil

CAUTION: For Use in Dry Feeds only. Not for use in liquid medicated feeds.

Directions For Use

Approved concentrations of bacitracin in Type C medicated feeds.

Species

Grams of bacitracin per ton

Indications For Use

Feeding Directions

Broiler and replacement chickens, growing turkeys, growing pheasants

4-50

For increased rate of weight gain and improved feed efficiency.

Feed as the sole ration throughout the feeding period.

Broiler and replacement chickens

50

For the prevention of mortality caused by necrotic enteritis associated with Clostridium perfringens.

Feed as the sole ration for 28 to 35 days, starting from the time chicks are placed for brooding.

Growing Quail

5-20

For increased rate of weight gain and improved feed efficiency in quail not over 5 weeks of age.

Feed as the sole ration through 5 weeks of age.

Beef steers and heifers fed in confinement for slaughter

70 mg/head/day

For reduction in the number of liver condemnations due to abscesses.

Feed as the sole ration throughout the feeding period.

250 mg/head/day

For reduction in the number of liver condemnations due to abscesses.

Feed as the sole ration for 5 days then discontinue for subsequent 25 days, repeat the pattern during the feeding period.

.Mixing Directions

Prepare an intermediate preblend containing 5 grams of bacitracin per pound by mixing 1.0 lb of Pennitracin MD 50G with 9.0 lbs of unmedicated feed ingredient(s), then add 0.8 to 10 lbs of the intermediate preblend per ton of the finished feed to obtain the appropriate g/ton concentration of the Type C medicated feed.

Prepare Type B medicated feeds for chickens, turkeys, pheasants, or beef cattle containing 51 – 50,000 grams of bacitracin per ton by mixing 1.02 – 1,000 lbs of Pennitracin MD 50G with 1,998.98 – 1,000 lbs of unmedicated feed.

CAUTION: For Use in Dry Feeds only. Not for use in liquid medicated feeds.

WARNINGS

Withdrawal Periods:

No withdrawal period is required when used according to labeling.

User Safety Warnings:

Not for use in humans. Keep out of reach of children.

Store at or below 25ºC (77ºF)

Lot Number and Expiration Date: Both the Lot number and expiry date is provided on the front panel of the bag.

QUESTIONS/COMMENTS? Contact Pharmgate Animal Health LLC at 1-800-380-6099 or www.pharmgate.com. To report side effects, contact Pharmgate Animal Health LLC at 1-833-531-0114. For additional information about reporting side effects for animal drugs, contact FDA at 1-888-FDA-VETS or http://www.fda.gov/reportanimalae.

Approved by FDA under NADA # 141-137

Pennitracin MD 50G® is a registered trademark of Pharmgate Inc.

Marketed by:
PHARMGATE ANIMAL HEALTH LLC
14040 Industrial Road
Omaha, NE 68144

Take Time |  | Observe Directions

PRINCIPAL DISPLAY PANEL - 22.68 Kg Bag

Pennitracin MD 50G®

(Bacitracin Type A medicated article)

For further manufacturing only.

See mixing directions, claims, cautions
and warnings on back panel.

Restricted Drug (California) - Use Only as Directed.

Net wt. 50 LB (22.68 Kg)

Pharmgate
ANIMAL HEALTH